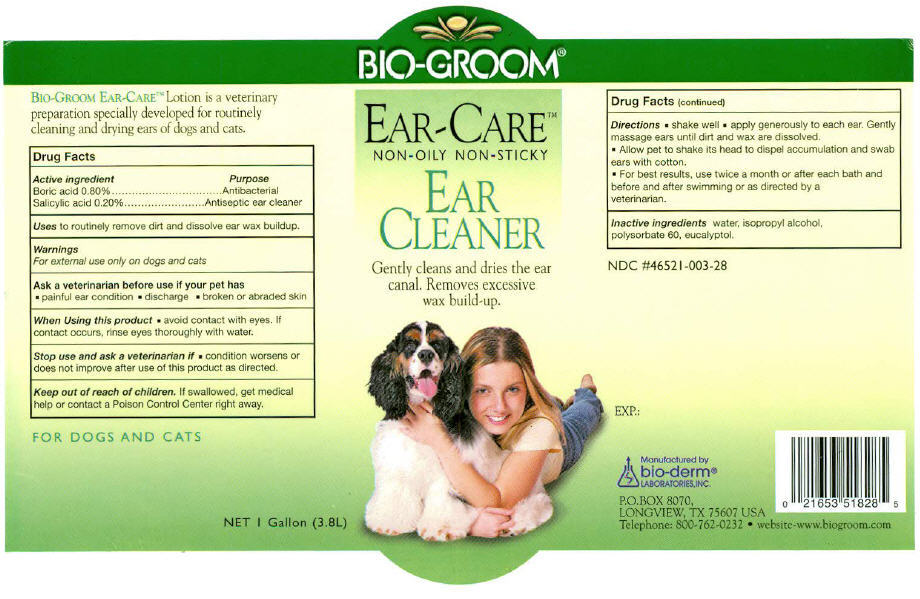 DRUG LABEL: Bio-Groom 
NDC: 46521-003 | Form: SOLUTION
Manufacturer: Bio-Derm Laboratories Inc.
Category: animal | Type: OTC ANIMAL DRUG LABEL
Date: 20110610

ACTIVE INGREDIENTS: BORIC ACID 0.8 mg/100 mL; SALICYLIC ACID 0.2 mg/100 mL
INACTIVE INGREDIENTS: WATER; ISOPROPYL ALCOHOL; POLYSORBATE 60; EUCALYPTOL

BIO-GROOM®
EAR-CARE™
NON OILY-NON STICKY
EAR CLEANER

Drug Facts

ACTIVE INGREDIENT

Active Ingredient | Purpose
Boric acid 0.80% | Antibacterial
Salicylic acid 0.20% | Antiseptic ear cleaner

Uses

to routinely remove dirt and dissolve ear wax buildup.

Warnings

For external use only on dogs and cats

Ask a veterinarian before use if your pet has

- painful ear condition
- discharge
- broken or abraded skin

When Using this product

- avoid contact with eyes. If contact occurs, rinse eyes thoroughly with water.

Stop use and ask a veterinarian if

- condition worsens or does not improve after use of this product as directed.

Keep out of reach of children. If swallowed, get medical help or contact a Poison Control Center right away.

Directions

- shake well
- apply generously to each ear. Gently massage ears until dirt and wax are dissolved.
- Allow pet to shake its head to dispel accumulation and swab ears with cotton.
- For best results, use twice a month or after each bath and before and after swimming or as directed by a veterinarian.

Inactive ingredients

water, isopropyl alcohol, polysorbate 60, eucalyptol.

Manufactured by
bio-derm®
LABORATORIES, INC.
P.O.BOX 8070,
LONGVIEW, TX 75607 USA

PRINCIPAL DISPLAY PANEL - 3.8L Bottle Label

BIO-GROOM®

EAR-CARE™
NON-OILY NON-STICKY

EAR
CLEANER

Gently cleans and dries the ear
canal. Removes excessive
wax build-up.